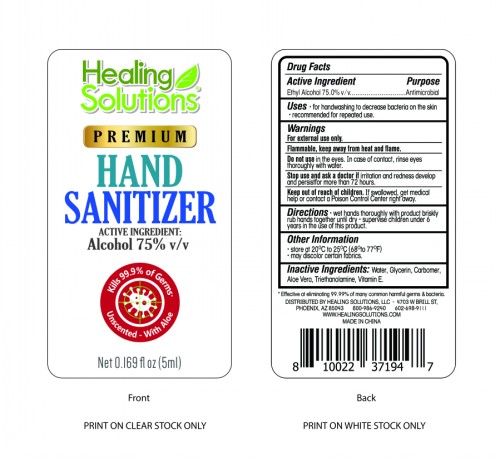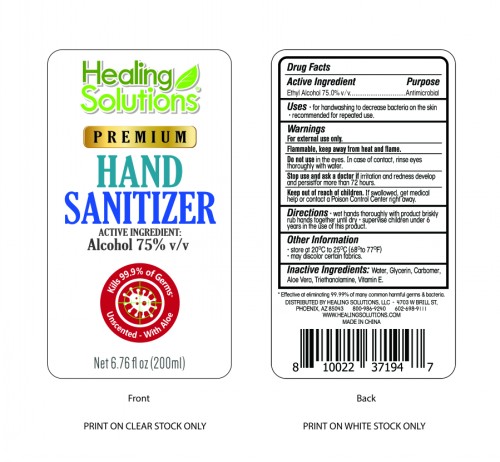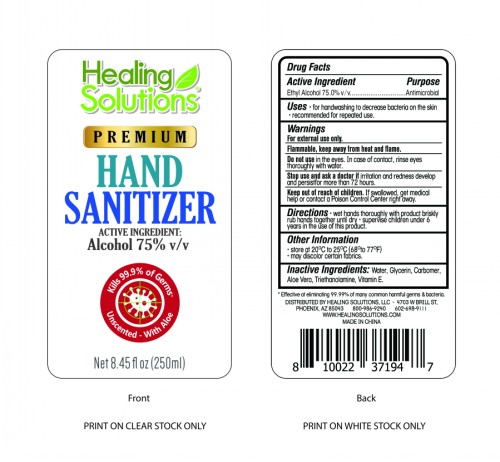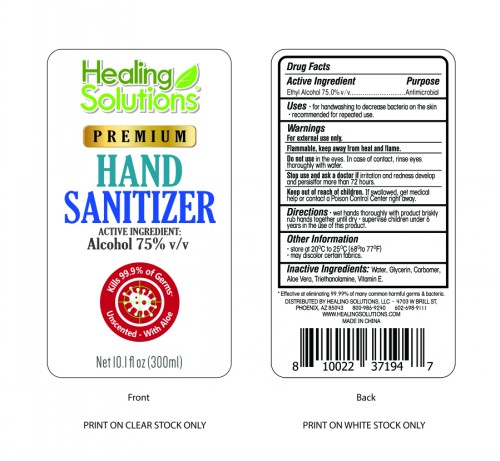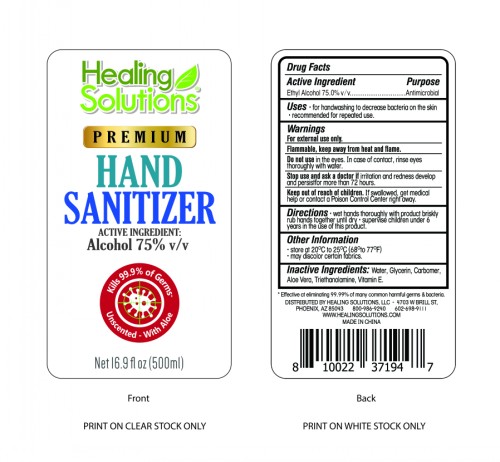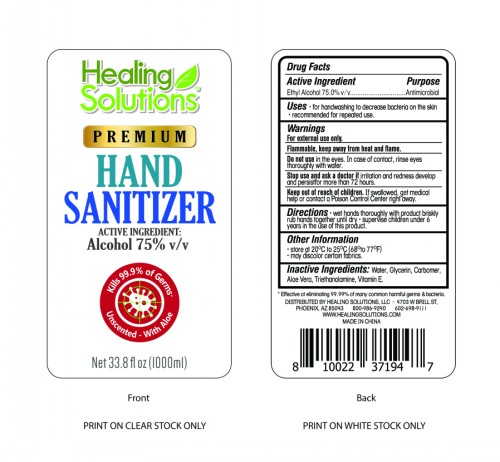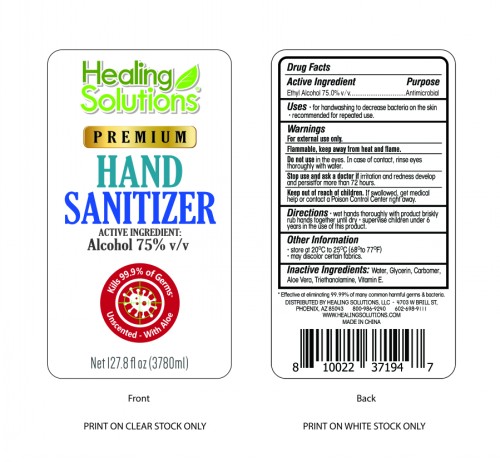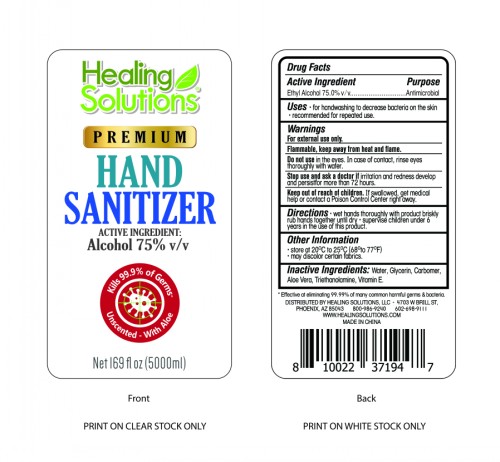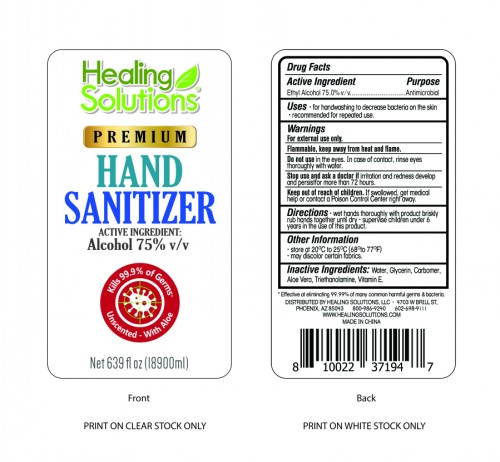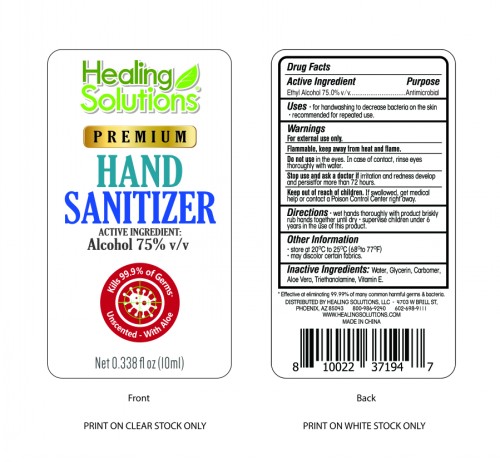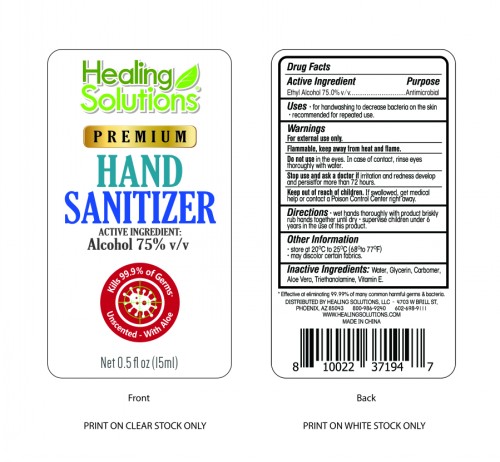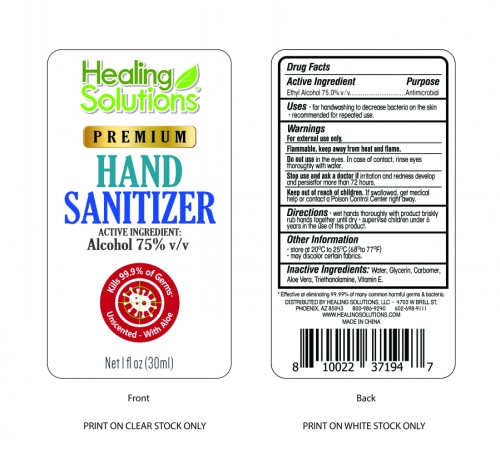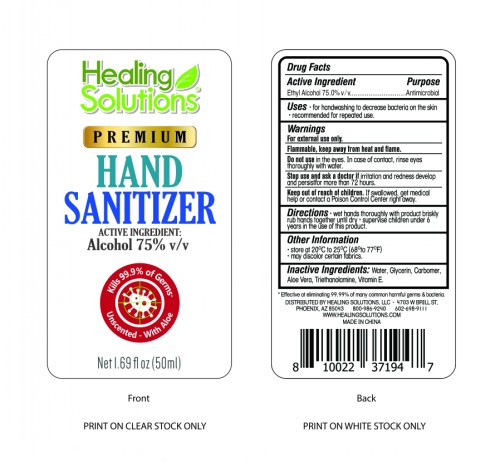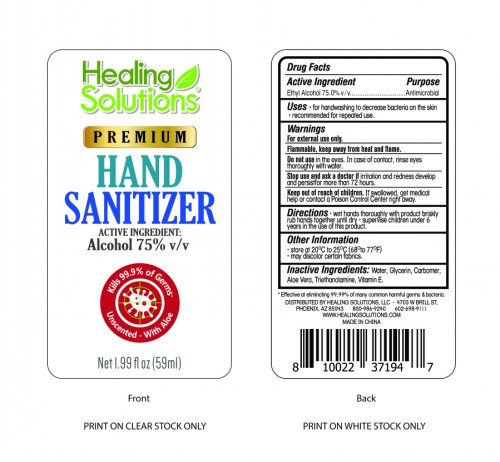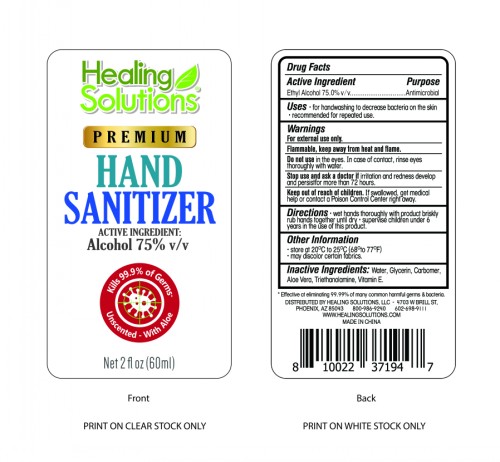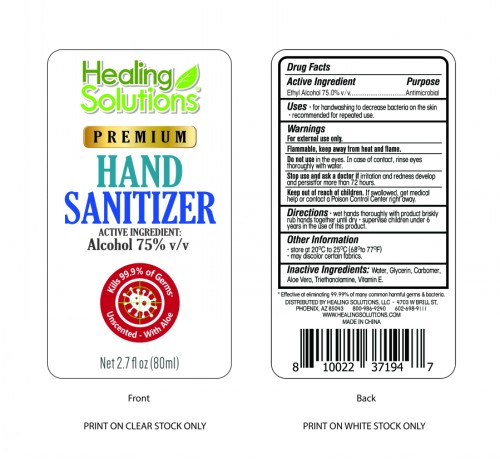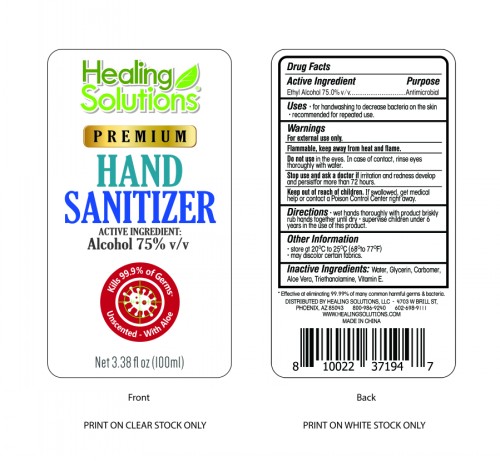 DRUG LABEL: Hand  Sanitizer
NDC: 78403-001 | Form: GEL
Manufacturer: Guangzhou Cangty Biotechnology Co., Ltd.
Category: otc | Type: HUMAN OTC DRUG LABEL
Date: 20200516

ACTIVE INGREDIENTS: ALCOHOL 75 mL/100 mL
INACTIVE INGREDIENTS: GLYCERIN; CARBOMER HOMOPOLYMER, UNSPECIFIED TYPE; ALOE VERA LEAF; TROLAMINE; WATER; .ALPHA.-TOCOPHEROL

HAND SANITIZER

Active Ingredient

Ethyl Alcohol 75.0%v/v

Purpose

Antimicrobial

Uses

for handwashing to decrease bacteria on the skin.

recommended for repeated use.

Warnings

For external use only.Flammable. Keep away from heat and flame.

Do not use

in the eyes.In case of contact,rinse eyes thoroughly with water.

Stop use and ask a doctor if

irritation and redness develop and persistfor more than 72 hours.

Keep out of reach for children

If swallowed,get medical help or contact a Poison Control Center right away.

Directions

wet hands thoroughly with product briskly rub hands together until dry. Supervise children under 6 years in the use of this product.

Other Information

store at 20℃ to 25℃(68° to 77°F）

may discolor certain fabrics.

Inactive ingredients

Water,Glycerin, Carbomer,Aloe Vera,Triethanolamine,Vitamin E.